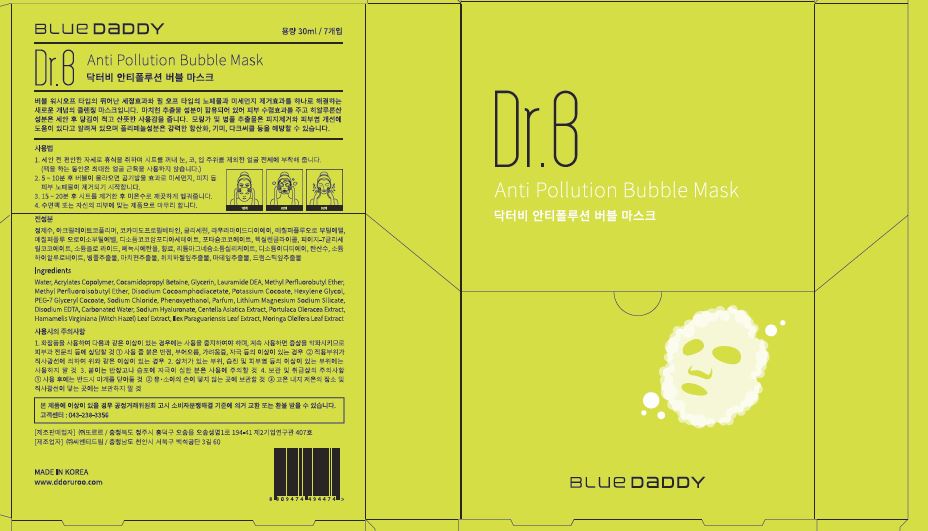 DRUG LABEL: Dr. B Anti Pollution Bubble Mask
NDC: 71484-0006 | Form: LIQUID
Manufacturer: Ddoruroo Co., Ltd.
Category: otc | Type: HUMAN OTC DRUG LABEL
Date: 20171220

ACTIVE INGREDIENTS: GLYCERIN 4 g/100 mL
INACTIVE INGREDIENTS: WATER

Drug Facts

ACTIVE INGREDIENT

glycerin

INACTIVE INGREDIENT

water, sodium chloride, carbonated water, etc

PURPOSE

SKIN PROTECTANT

KEEP OUT OF REACH OF THE CHILDREN

INDICATIONS AND USAGE

① Put the sheet on the face in a comfortable posture without cleansing
② After 5 to 10 minutes, bubbles begin to remove skin wastes, sebum and fine dust
③ Wait 5 to 10 more minutes, remove the sheet then wash it with lukewarm water or take a shower
④ Finish with appropriate toner

WARNINGS

1. Do not use in the following cases(Eczema and scalp wounds)
2.Side Effects
1)Due to the use of this druf if rash, irritation, itching and symptopms of hypersnesitivity occur dicontinue use and consult your phamacisr or doctor
3.General Precautions
1)If in contact with the eyes, wash out thoroughty with water If the symptoms are servere, seek medical advice immediately
2)This product is for exeternal use only. Do not use for internal use
4.Storage and handling precautions
1)If possible, avoid direct sunlight and store in cool and area of low humidity
2)In order to maintain the quality of the product and avoid misuse
3)Avoid placing the product near fire and store out in reach of children

DOSAGE AND ADMINISTRATION

for external use only